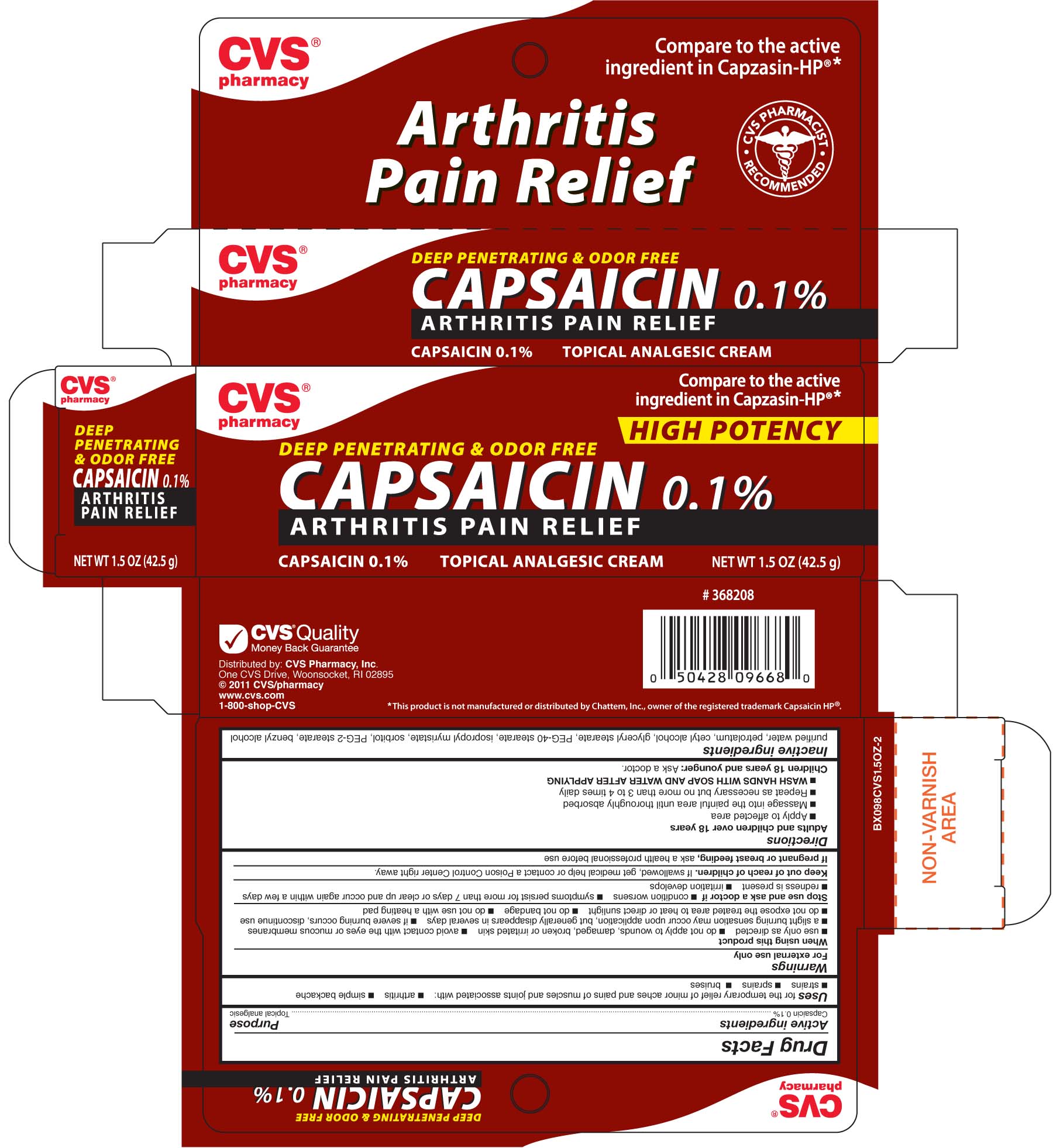 DRUG LABEL: CVS Capsaicin
NDC: 59779-622 | Form: CREAM
Manufacturer: CVS Pharmacy
Category: otc | Type: HUMAN OTC DRUG LABEL
Date: 20100708

ACTIVE INGREDIENTS: CAPSAICIN 75 mg/1 g
INACTIVE INGREDIENTS: DIGLYCOL STEARATE; PETROLATUM; POLYOXYL 40 STEARATE; BENZYL ALCOHOL; CETYL ALCOHOL; SORBITOL; ISOPROPYL MYRISTATE; WATER

DRUG FACTS

Active ingredient Purpose
Capsaicin 0.1%............................................Topical analgesic

PURPOSE

Uses for the temporary relieves of minor aches and pains of muscles and joints associated with:
- arthritis - simple backache - strains - bruises

Keep out of reach of children. If case of overdose or allergic reaction, seek medical attention or contact
a Poison Control Center right away.

INDICATIONS AND USAGE

Uses for the temporary relieves of minor aches and pains of muscles and joints associated with:
- arthritis - simple backache - strains - bruises

Warnings
For external use only
When using this product
- use only as directed - do not apply to wounds, damaged, broken or irritated skin - avoid contact
with the eyes or mucous membranes - a slight burning sensation may occur upon application, but
generally disappears in several days - if severe burning occurs, discontinue use - do not expose
the treated area to heat or direct sunlight - do not bandage - do not use with heating pad
Stop use and consult a dentist or doctor if:
- condition worsens - symptoms persist for more than 7 days or clear up and occur again within a few days
- redness is present - irritation develops
Keep out of the reach of children.In case of overdose or allergic reaction,
seek medical attention or contact a Poison Control Center right away.
If pregnant or breast feeding, ask a health professional before use.

Directions
Adults and children over 18 years
- apply to affected area
- Massage into the painful area until thoroughly absorbed
- Repeat as necessary, but no more than 3 to 4 times daily
- WASH HANDS WITH SOAP AND WATER AFTER APPLYING
Children 18 years and younger: ask a doctor.

Inactive Ingredients
purified water, petrolatum, cetyl alcohol glyceryl stearate, PEG-40 stearate, isopropyl myristate, sorbitol, PEG-2 stearate, benzyl alcohol